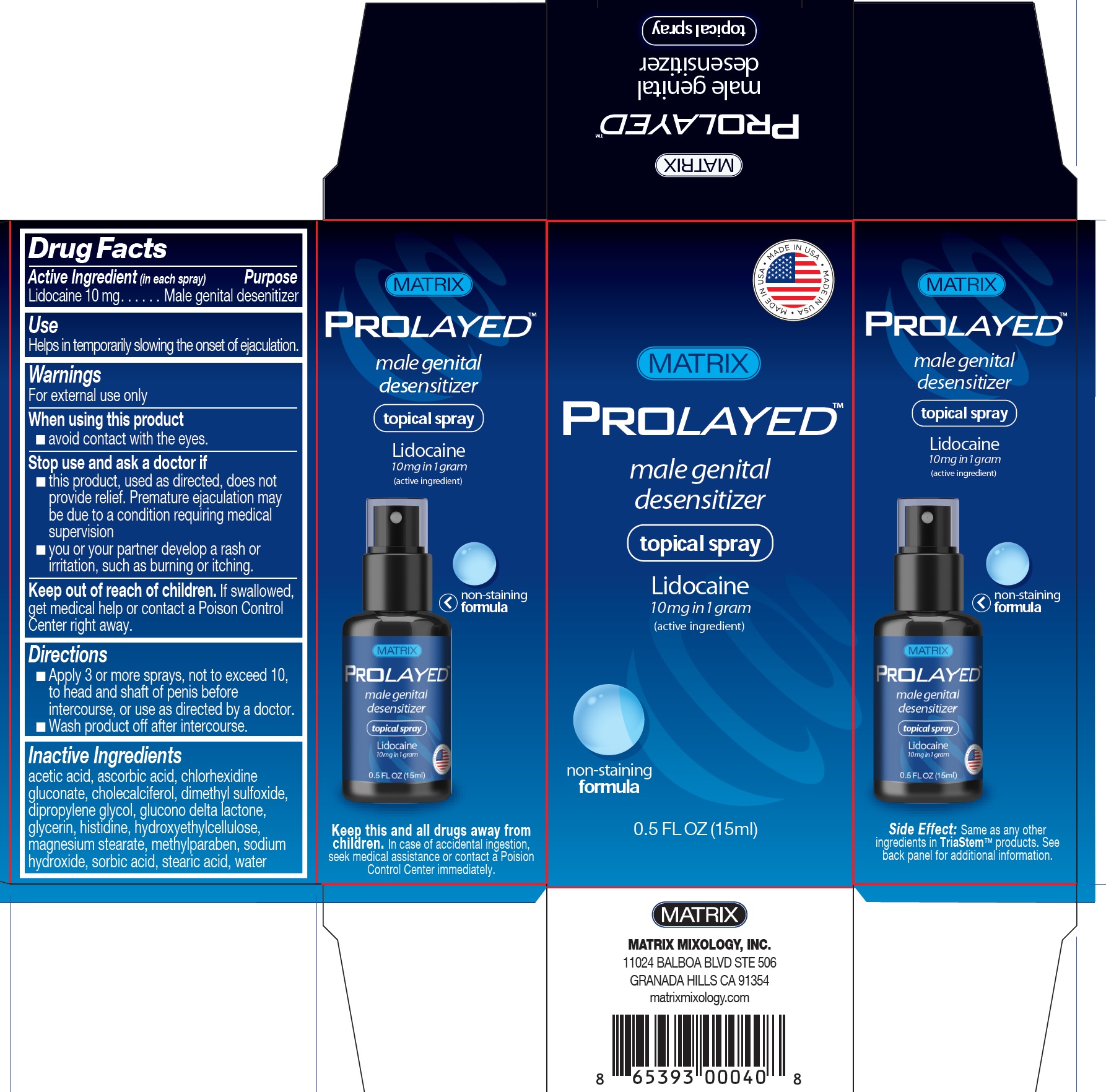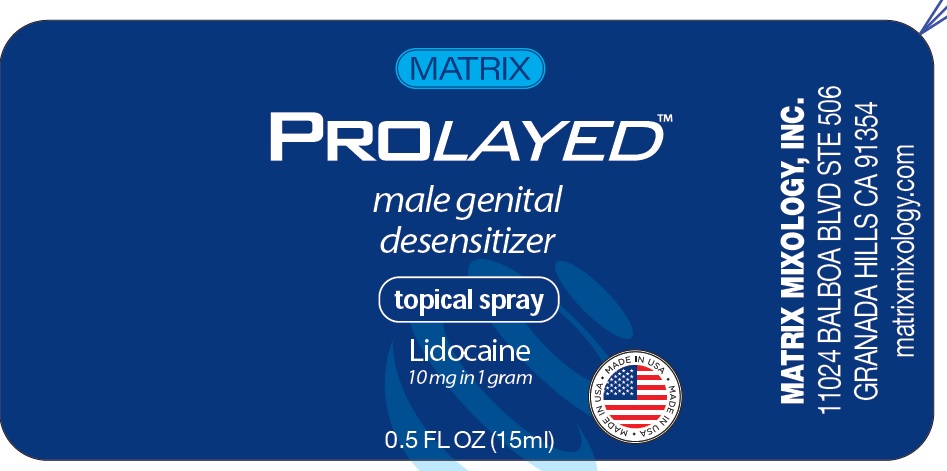 DRUG LABEL: Prolayed
NDC: 79218-001 | Form: SPRAY
Manufacturer: MATRIX MIXOLOGY, INC
Category: otc | Type: HUMAN OTC DRUG LABEL
Date: 20231201

ACTIVE INGREDIENTS: LIDOCAINE 10 mg/1 mL
INACTIVE INGREDIENTS: ACETIC ACID; ASCORBIC ACID; CHLORHEXIDINE GLUCONATE; CHOLECALCIFEROL; DIMETHYL SULFOXIDE; DIPROPYLENE GLYCOL; GLUCONOLACTONE; GLYCERIN; HISTIDINE; HYDROXYETHYL CELLULOSE, UNSPECIFIED; MAGNESIUM STEARATE; METHYLPARABEN; SODIUM HYDROXIDE; SORBIC ACID; STEARIC ACID; WATER

Prolayed

Active Ingredient (in each spray)

Lidocaine 10 mg

Purpose

Male genital desenitizer

Use

Helps in temporarily slowing the onset of ejaculation.

Warnings

For external use only

When using this product

- avoid contact with the eyes.

Stop use and ask a doctor if

- this product, used as directed, does not provide relief. Premature ejaculation may be due to a condition requiring medical supervision
- you or your partner develop a rash or irritation, such as burning or itching.

Keep out of reach of children

If swallowed, get medical help or contact a Poison Control Center right away.

Directions

- Apply 3 or more sprays, not to exceed 10, to head and shaft of penis before intercourse, or use as directed by a doctor.
- Wash product off after intercourse.

Inactive Ingredients

acetic acid, ascorbic acid, chlorhexidine gluconate, cholecalciferol, dimethyl sulfoxide, dipropylene glycol, glucono delta lactone, glycerin, histidine, hydroxyethylcellulose, magnesium stearate, methylparaben, sodium hydroxide, sorbic acid, stearic acid, water